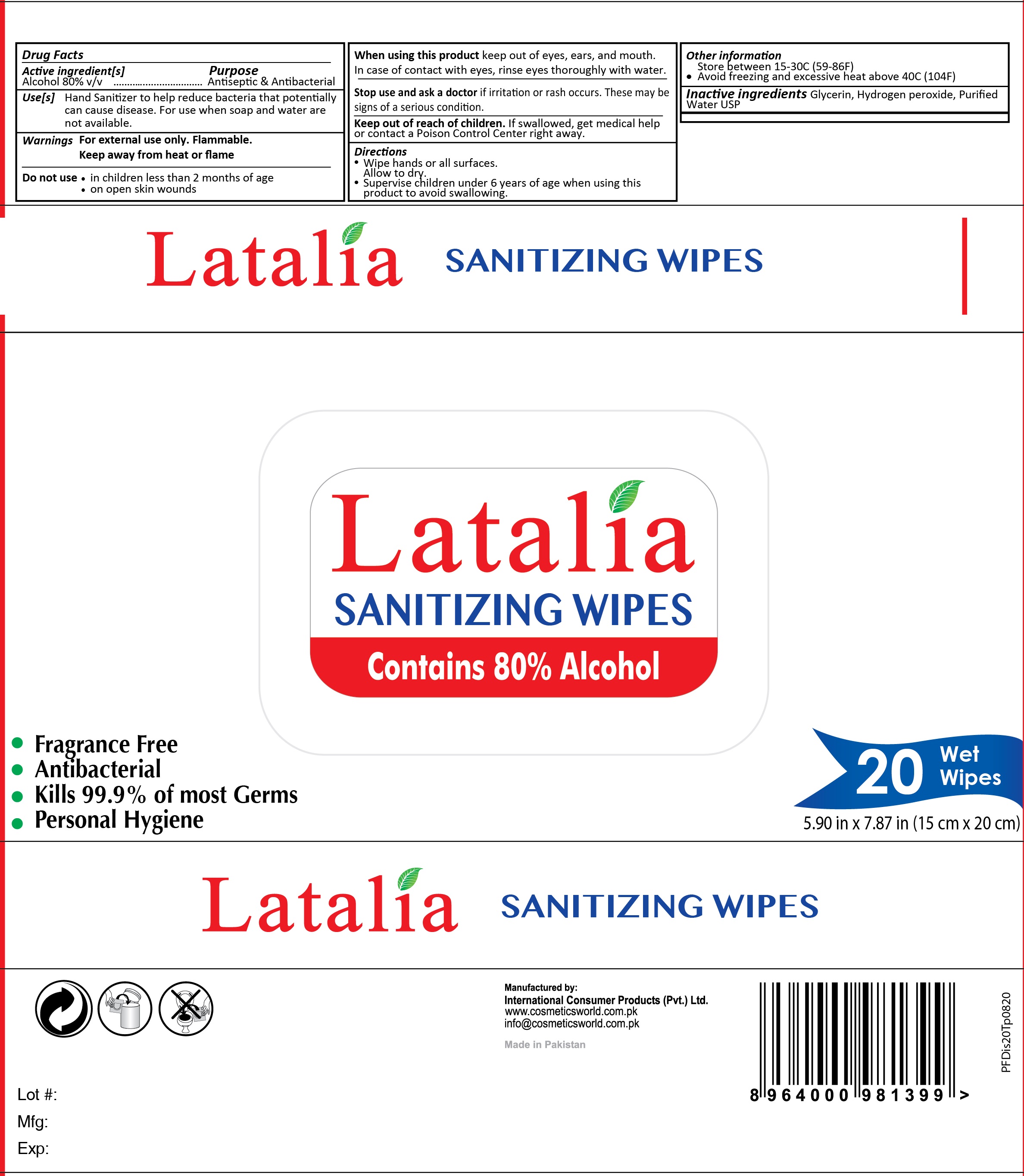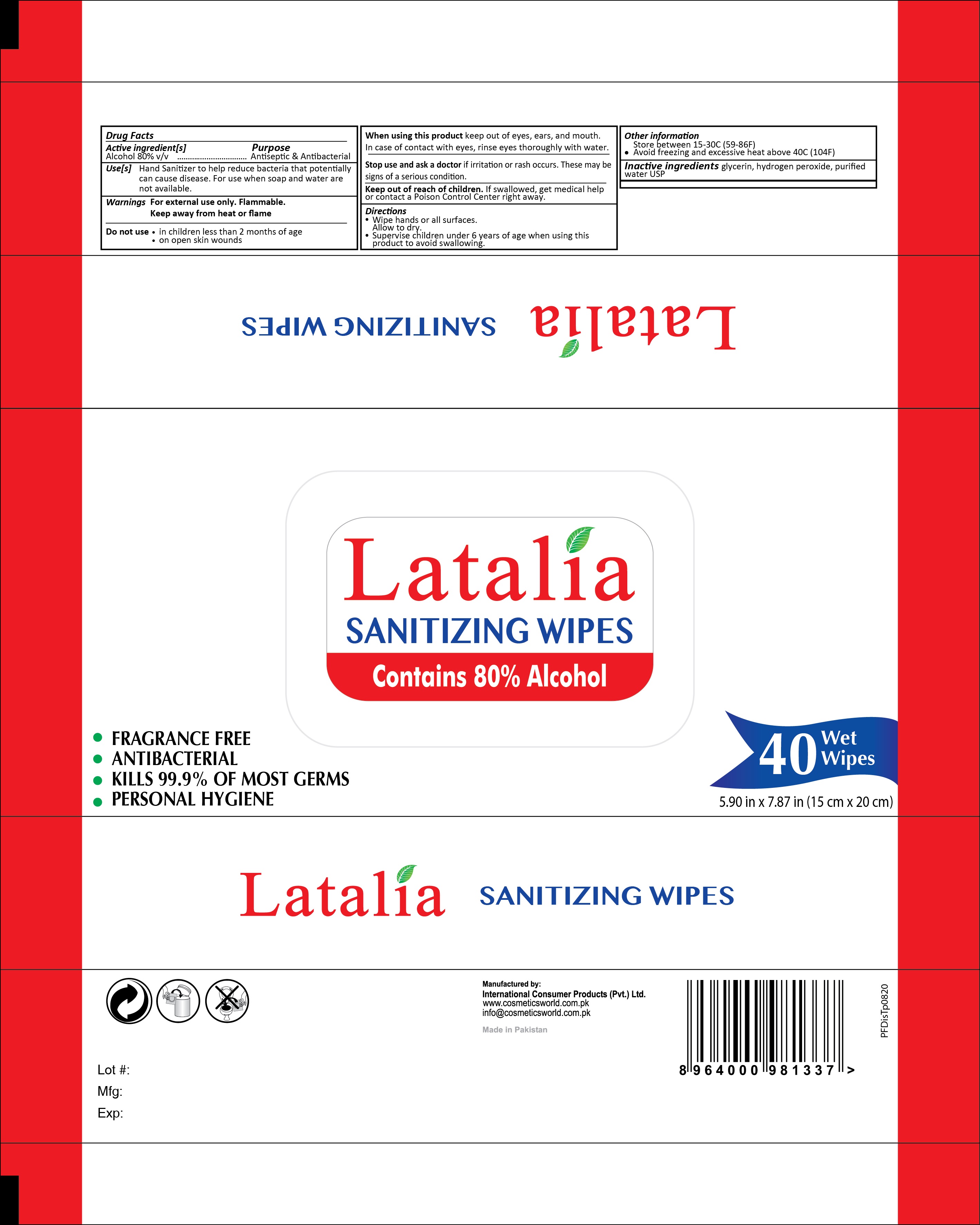 DRUG LABEL: Latalia Sanitizing Wipes
NDC: 80016-003 | Form: CLOTH
Manufacturer: INTERNATIONAL CONSUMER PRODUCTS (PVT) LTD
Category: otc | Type: HUMAN OTC DRUG LABEL
Date: 20240110

ACTIVE INGREDIENTS: ALCOHOL 0.8 mL/1 mL
INACTIVE INGREDIENTS: HYDROGEN PEROXIDE; WATER; GLYCERIN

Latalia Sanitizing Wipes

Active ingredient[s]

Alcohol 80% v/v

Purpose

Antiseptic & Antibacterial

Use[s]

Hand Sanitizer to help reduce bacteria that potentially can cause disease. For use when soap and water are not available.

Warnings

For external use only. Flammable.
Keep away from heat or flame

Do not use

- in children less than 2 months of age
- on open skin wounds

When using this product

keep out of eyes, ears, and mouth. In case of contact with eyes, rinse eyes thoroughly with water.

Stop use and ask a doctor

if irritation or rash occurs. These may be signs of a serious condition.

Keep out of reach of children.

If swallowed, get medical help or contact a Poison control Center right away.

Directions

- Wipe hands or all surfaces. Allow to dry.
- Supervise children under 6 years of age when using this product to avoid swallowing.

Other information

Store between 15-30C (59-86F)

- Avoid freezing and excessive heat above 40C (104F)

Inactive ingredients

Glycerin, Hydrogen peroxide, Purified Water USP